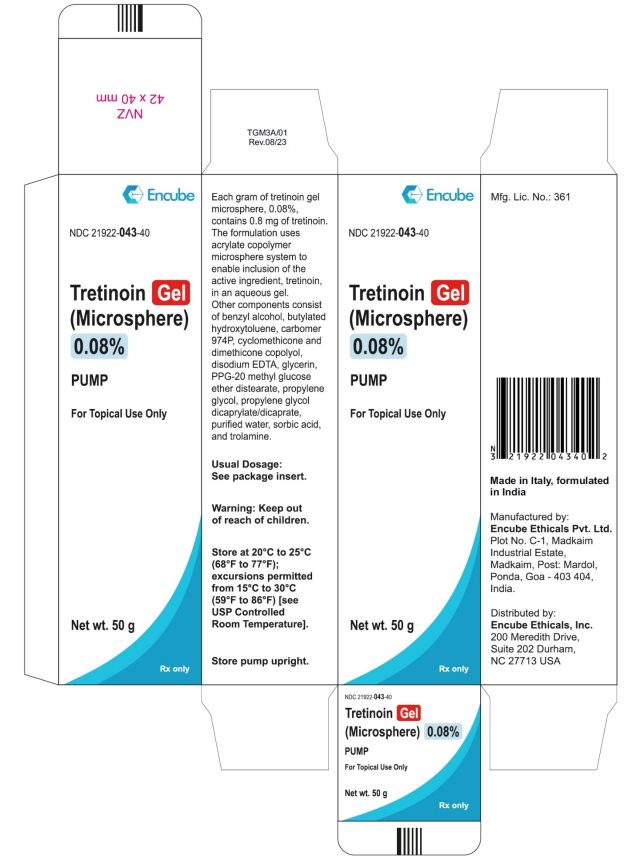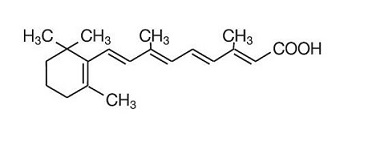 DRUG LABEL: TRETINOIN
NDC: 21922-043 | Form: GEL
Manufacturer: Encube Ethicals, Inc.
Category: prescription | Type: HUMAN PRESCRIPTION DRUG LABEL
Date: 20250912

ACTIVE INGREDIENTS: TRETINOIN 0.8 mg/1 g
INACTIVE INGREDIENTS: BENZYL ALCOHOL; BUTYLATED HYDROXYTOLUENE; Carbomer Homopolymer Type B (Allyl Pentaerythritol Crosslinked); CYCLOMETHICONE; EDETATE DISODIUM; GLYCERIN; PPG-20 METHYL GLUCOSE ETHER DISTEARATE; PROPYLENE GLYCOL; WATER; SORBIC ACID; TROLAMINE

HIGHLIGHTS OF PRESCRIBING INFORMATION

These highlights do not include all the information needed to use TRETINOIN GEL (MICROSPHERE) safely and effectively. See full prescribing information for TRETINOIN GEL (MICROSPHERE).
TRETINOIN gel (microsphere), for topical use.
Initial U.S. Approval: 1971

1 INDICATIONS AND USAGE

Tretinoin gel (microsphere) is a retinoid, indicated for topical treatment of acne vulgaris.(1)

2 DOSAGE AND ADMINISTRATION

- Apply a thin layer of tretinoin gel microsphere once daily, before bedtime, to skin where lesions occur. Keep away from eyes, mouth, nasal creases, and mucous membranes. (2)
- Not for oral, ophthalmic, or intravaginal use. (2)

3 DOSAGE FORMS AND STRENGTHS

Gel, 0.08%, (3)

4 CONTRAINDICATIONS

None. (4)

5 WARNINGS AND PRECAUTIONS

- Tretinoin gel (microsphere) should not be used on eczematous or sunburned skin due to potential for severe irritation. (5.1, 5.2)
- Avoid unprotected exposure to sunlight including sunlamps (UV light), when using tretinoin gel (microsphere) due to potential for increased photosensitization. Use sunscreen of at least SPF 15 and protective clothing during exposure. (5.2)
- Avoid use of tretinoin gel (microsphere) with weather extremes, such as wind or cold due to potential for increased irritation. (5.2)

6 ADVERSE REACTIONS

Most common adverse reactions are skin pain, pruritus, skin irritation/subcutaneous irritation, pharyngitis, and erythema. (6.1)
To report SUSPECTED ADVERSE REACTIONS, contact Encube Ethicals Private Limited at 1-833-285-4151 or FDA at 1-800-FDA-1088 or www.fda.gov/medwatch.

8 USE IN SPECIFIC POPULATIONS

Tretinoin gel (microsphere) should be used during pregnancy only if the potential benefit justifies the potential risk to the fetus. There are no adequate and well-controlled studies in pregnant and nursing women. (8.1)

See 17 for PATIENT COUNSELING INFORMATION and FDA-approved patient labeling.

FULL PRESCRIBING INFORMATION

1 INDICATIONS AND USAGE

Tretinoin gel (microsphere) is a retinoid indicated for topical application in the treatment of acne vulgaris.

2 DOSAGE AND ADMINISTRATION

For topical use only. Not for ophthalmic, oral, or intravaginal use.
Tretinoin gel (microsphere) should be applied once a day, in the evening, to the skin where acne lesions appear, using enough to cover the entire affected area in a thin layer. Areas to be treated should be cleansed thoroughly before the medication is applied. If medication is applied excessively, no more rapid or better results will be obtained and marked redness, peeling, or discomfort may occur. A transitory feeling of warmth or slight stinging may be noted on application. In cases where it has been necessary to temporarily discontinue therapy or to reduce the frequency of application, therapy may be resumed or the frequency of application increased as the patient becomes able to tolerate the treatment. Frequency of application should be closely monitored by careful observation of the clinical therapeutic response and skin tolerance. Efficacy has not been established for less than once daily dosing frequencies.
During the early weeks of therapy, an apparent exacerbation of inflammatory lesions may occur. If tolerated, this should not be considered a reason to discontinue therapy [seeAdverse Reactions (6.1)].
Therapeutic results may be noticed after two weeks, but more than seven weeks of therapy are required before consistent beneficial effects are observed.
Tretinoin gel (microsphere) should be kept away from the eyes, the mouth, paranasal creases of the nose, and mucous membranes.
Patients treated with tretinoin gel microsphere may use cosmetics.
Concomitant topical medication, medicated or abrasive soaps and cleansers, products that have a strong drying effect, products with high concentrations of alcohol, astringents, or spices should be used with caution because of possible interaction with tretinoin. Avoid contact with the peel of limes. Particular caution should be exercised with the concomitant use of topical over-the-counter acne preparations containing benzoyl peroxide, sulfur, resorcinol, or salicylic acid with tretinoin gel (microsphere). It also is advisable to allow the effects of such preparations to subside before use of tretinoin gel (microsphere) is begun.

3 DOSAGE FORMS AND STRENGTHS

Tretinoin gel (microsphere) is a white to very pale yellow opaque gel. Tretinoin gel (microsphere) is available in strength: 0.08%.
Each gram of tretinoin gel (microsphere), 0.08%, contains 0.8 mg of tretinoin.

4 CONTRAINDICATIONS

None.

5 WARNINGS AND PRECAUTIONS

5.1 Local Irritation

The skin of certain individuals may become excessively dry, red, swollen, or blistered.
Tretinoin has been reported to cause severe irritation on eczematous skin and should be used with utmost caution in patients with this condition.
If the degree of irritation warrants, patients should be directed to temporarily reduce the amount or frequency of application of the medication, discontinue use temporarily, or discontinue use all together. Efficacy at reduced frequencies of application has not been established. If a reaction suggesting sensitivity occurs, use of the medication should be discontinued.
To help limit skin irritation, patients must

i. wash the treated skin gently, using a mild, non-medicated soap, and pat it dry, and

ii. avoid washing the treated skin too often or scrubbing it hard when washing.

Patients should apply a topical moisturizer if dryness is bothersome.

5.2 Exposure to Ultraviolet Light or Weather Extremes

Unprotected exposure to sunlight, including sunlamps (UV light) should be avoided or minimized during the use of tretinoin gel (microsphere) and patients with sunburn should be advised not to use the product until fully recovered because of heightened susceptibility to sunlight as a result of the use of tretinoin. Patients who may be required to have extended periods of UV exposure (e.g., due to occupation or sports), or those with inherent sensitivity to the sun, or those using medications that cause photosensitivity, should exercise particular caution. Use of sunscreen products (SPF 15 or higher) and protective clothing over treated areas are recommended when exposure cannot be avoided [seeNonclinical Toxicology (13.1)].

Weather extremes, such as wind or cold, also may be irritating to tretinoin-treated skin.

6 ADVERSE REACTIONS

6.1 Clinical Trials Experience

Because clinical trials are conducted under widely varying conditions, adverse reaction rates observed in the clinical trials of a drug cannot be directly compared to rates in the clinical trials of another drug and may not reflect the rates observed in practice.

Clinical Trials in Subjects with Acne

In separate clinical trials for each concentration, acne subjects treated with tretinoin gel (microsphere), 0.1% or 0.04%, over the twelve-week period showed that cutaneous irritation scores for erythema, peeling, dryness, burning/stinging, or itching peaked during the initial two weeks of therapy, decreasing thereafter.

Approximately half of the subjects treated with tretinoin gel (microsphere), 0.04%, had cutaneous irritation at Week 2. Of those subjects who did experience cutaneous side effects, most had signs or symptoms that were mild in severity (severity was ranked on a 4-point ordinal scale: 0=none, 1=mild, 2=moderate, and 3=severe). Less than 10% of patients experienced moderate cutaneous irritation and there was no severe irritation at Week 2.

In trials of tretinoin gel (microsphere), 0.04%, throughout the treatment period the majority of subjects experienced some degree of irritation (mild, moderate, or severe) with 1% (2/225) of subjects having scores indicative of a severe irritation; 1.3% (3/225) of subjects treated with tretinoin gel (microsphere) 0.04%, discontinued treatment due to irritation, which included dryness in one patient and peeling and urticaria in another.

In trials of tretinoin gel (microsphere), 0.1%, no more than 3% of subjects had cutaneous irritation scores indicative of severe irritation; 6% (14/224) of subjects treated with tretinoin gel (microsphere), 0.1%, discontinued treatment due to irritation. Of these 14 subjects, four had severe irritation after 3 to 5 days of treatment, with blistering in one subject.

In a double-blind trial with 156 acne subjects comparing 12 weeks of treatment with tretinoin gel (microsphere) 0.04% or 0.1%, (78 subjects each group), the most frequently-reported adverse events affected the skin and subcutaneous tissue (15.4% in the 0.04% group, and 20.5% in the 0.1% group). The most prevalent of the dermatologic adverse events in the 0.04% group was skin irritation (6.4%); and in the 0.1% group skin burning (7.7%), erythema (5.1%), skin irritation (3.8%), and dermatitis (3.8%). Most adverse events were of mild intensity (63.4%), and 34.4% were moderate. One subject in each group had adverse events characterized as severe, neither were dermatologic findings and neither was characterized as related to drug by the investigator.

Trials in Subjects without Acne

In a half-face comparison trial conducted for up to 14 days in women with sensitive skin, but without acne, tretinoin gel (microsphere), 0.1%, was statistically less irritating than tretinoin cream, 0.1%. In addition, a cumulative 21- day irritation evaluation in subjects with normal skin showed that tretinoin gel (microsphere), 0.1%, had a lower irritation profile than tretinoin cream, 0.1%. The clinical significance of these irritation studies for patients with acne is not established.

Comparable effectiveness of tretinoin gel (microsphere), 0.1%, and tretinoin cream, 0.1%, has not been established. The lower irritancy of tretinoin gel (microsphere), 0.1%, in subjects without acne may be attributable to the properties of its vehicle. The contribution of decreased irritancy by the acrylate copolymer microsphere system has not been established. No irritation trials have been performed to compare tretinoin gel (microsphere), 0.04%, with either tretinoin gel (microsphere), 0.1%, or tretinoin cream, 0.1%.

6.2 Postmarketing Experience

The following adverse reactions have been identified during post-approval use of tretinoin gel (microsphere). Because these reactions are reported voluntarily from a population of uncertain size, it is not always possible to reliably estimate their frequency or establish a causal relationship to drug exposure.

Temporary hyper- or hypopigmentation has been reported with repeated application of tretinoin.

8 USE IN SPECIFIC POPULATIONS

8.1 Pregnancy

Pregnancy Category C

There are no adequate and well-controlled studies in pregnant women. Tretinoin gel (microsphere) should be used during pregnancy only if the potential benefit justifies the potential risk to the fetus.

Thirty human cases of temporally associated congenital malformations have been reported during two decades of clinical use of tretinoin products. Although no definite pattern of teratogenicity and no causal association has been established from these cases, five of the reports describe the rare birth defect category holoprosencephaly (defects associated with incomplete midline development of the forebrain). The significance of these spontaneous reports in terms of risk to the fetus is not known.

For purposes of comparison of the animal exposure to systemic human exposure, the MRHD applied topically is defined as 1 gram of tretinoin gel (microsphere)‚ 0.1%, applied daily to a 60 kg person (0.017 mg tretinoin/kg body weight).

Pregnant rats were treated with tretinoin gel (microsphere), 0.1%, at daily dermal doses of 0.5 to 1.0 mg/kg/day tretinoin on gestation days 6-15. Alterations were seen in vertebrae and ribs of offspring at 5 to 10 times the MRHD based on the body surface area (BSA) comparison.

Pregnant New Zealand White rabbits were treated with tretinoin gel (microsphere), 0.1%, at daily dermal doses of 0.2, 0.5, and 1.0 mg/kg/day tretinoin on gestation days 7-19. Doses were administered topically for 24 hours a day while wearing Elizabethan collars to prevent ingestion of the drug. Increased incidences of certain alterations, including domed head and hydrocephaly, typical of retinoid-induced fetal malformations in this species, were observed at 0.5 and 1.0 mg/kg/day. Similar malformations were not observed at 0.2 mg/kg/day, 4 times the MRHD based on BSA comparison. Other pregnant rabbits exposed topically for six hours per day to 0.5 or 1.0 mg/kg/day tretinoin while restrained in stocks to prevent ingestion, did not show any malformations at doses up to 19 times (1.0 mg/kg/day) the MRHD based on BSA comparison, but fetal resorptions were increased at 0.5 mg/kg (10 times the MRHD based on BSA comparison).

Oral tretinoin has been shown to cause malformations in rats, mice, rabbits, hamsters, and nonhuman primates.

Tretinoin induced fetal malformations in Wistar rats when given orally at doses greater than 1 mg/kg/day (10 times the MRHD based on BSA comparison). In the cynomolgus monkey, fetal malformations were reported for doses of 10 mg/kg/day but none were observed at 5 mg/kg/day (95 times the MRHD based on BSA comparison), although increased skeletal variations were observed at all doses. Dose-related increases in embryolethality and abortion also were reported. Similar results have also been reported in pigtail macaques.

In oral peri- and postnatal development studies in rats with tretinoin, decreased survival of neonates and growth retardation were observed at doses in excess of 2 mg/kg/day (19 times the MRHD based on BSA comparison).

Nonteratogenic effects on fetus

Oral tretinoin has been shown to be fetotoxic in rats when administered at doses 24 times the MRHD based on BSA comparison.

Topical tretinoin has been shown to be fetotoxic in rabbits when administered at doses 10 times the MRHD based on BSA comparison.

8.3 Nursing Mothers

It is not known whether tretinoin and/or its metabolites are excreted in human milk. Because many drugs are excreted in human milk, caution should be exercised when tretinoin gel (microsphere) is administered to a nursing woman.

8.4 Pediatric Use

Safety and effectiveness in children below the age of 12 have not been established.

8.5 Geriatric Use

Safety and effectiveness in a geriatric population have not been established. Clinical trials of tretinoin gel (microsphere), 0.1% and 0.04%, did not include sufficient numbers of subjects aged 65 and over to determine whether they responded differently from younger subjects.

10 OVERDOSAGE

Oral ingestion of large amounts of the drug may lead to the same side effects as those associated with excessive oral intake of Vitamin A.

11 DESCRIPTION

Tretinoin gel (microsphere), 0.08% is a white to very pale yellow opaque gel for topical treatment of acne vulgaris.

Chemically, tretinoin is all-trans-retinoic acid, also known as (all-E)-3,7-dimethyl-9-(2,6,6-trimethyl-1- cyclohexen-1-yl)-2,4,6,8-nonatetraenoic acid. It is a member of the retinoid class of compounds and a metabolite of naturally occurring Vitamin A. Tretinoin has a molecular weight of 300.44, a molecular formula of C20H28O2 and the following chemical structure:

Each gram of tretinoin gel (microsphere), 0.08%, contains 0.8 mg of tretinoin.

The formulation uses acrylate copolymer microsphere system to enable inclusion of the active ingredient, tretinoin, in an aqueous gel. Other components consist of benzyl alcohol, butylated hydroxytoluene, carbomer 974P, cyclomethicone and dimethicone copolyol, disodium EDTA, glycerin, PPG-20 methyl glucose ether distearate, propylene glycol, propylene glycol dicaprylate/dicaprate, purified water, sorbic acid, and trolamine.

12 CLINICAL PHARMACOLOGY

12.1 Mechanism of Action

Although tretinoin activates three members of the retinoic acid (RAR) nuclear receptors (RARα, RARβ, and RARγ) which may act to modify gene expression, subsequent protein synthesis, and epithelial cell growth and differentiation, it has not been established whether the clinical effects of tretinoin are mediated through activation of retinoic acid receptors and/or other mechanisms.

The exact mode of action of tretinoin is unknown. Current evidence suggests that topical tretinoin decreases cohesiveness of follicular epithelial cells with decreased microcomedone formation. Additionally, tretinoin stimulates mitotic activity and increased turnover of follicular epithelial cells causing extrusion of the comedones.

12.3 Pharmacokinetics

Tretinoin is a metabolite of Vitamin A metabolism in man. Percutaneous absorption, as determined by the cumulative excretion of radiolabeled drug into urine and feces, was assessed in 44 healthy men and women after single and repeated daily applications of 500 mg of a 0.1% tretinoin gel formulation. Estimates of in vivo bioavailability, mean (SD)%, following both single and multiple daily applications, for a period of 28 days with the 0.1% gel, were 0.82 (0.11)% and 1.41 (0.54)%, respectively. The plasma concentrations of tretinoin and its metabolites, 13-cis-retinoic acid, all-trans-4-oxo-retinoic acid, and 13-cis-4-oxo-retinoic acid, generally ranged from 1 to 3 ng/mL and were essentially unaltered after either single or multiple daily applications of tretinoin gel (microsphere), 0.1%, relative to baseline levels. Clinical pharmacokinetic studies have not been performed with tretinoin gel (microsphere), 0.08%, 0.06% and 0.04%.

13 NONCLINICAL TOXICOLOGY

13.1 Carcinogenesis, Mutagenesis, Impairment of Fertility

Dermal carcinogenicity testing has not been performed with tretinoin gel (microsphere), 0.1%, 0.08%, 0.06% or 0.04%.

In a 91-week dermal study in which CD-1 mice were administered 0.017% and 0.035% formulations of tretinoin, cutaneous squamous cell carcinomas and papillomas in the treatment area were observed in some female mice. These concentrations are near the tretinoin concentration of the 0.04% and 0.1% clinical formulations. A dose-related incidence of liver tumors in male mice was observed at those same doses. The maximum systemic doses associated with the administered 0.017% and 0.035% formulations are 0.5 and 1.0 mg/kg/day tretinoin, respectively. These doses are two and four times the MRHD based on BSA comparison.

The biological significance of these findings is not clear because they occurred at doses that exceeded the dermal maximally tolerated dose of tretinoin and because they were within the background natural occurrence rate for these tumors in this strain of mice.

There was no evidence of carcinogenic potential when 0.025 mg/kg/day of tretinoin was administered topically to mice (0.1 times the MRHD based on BSA comparison). Studies in hairless albino mice suggest that concurrent exposure to tretinoin may enhance the tumorigenic potential of carcinogenic doses of UVB and UVA light from a solar simulator. This effect has been confirmed in a later study in pigmented mice, and dark pigmentation did not overcome the enhancement of photocarcinogenesis by 0.05% tretinoin. Although the significance of these studies to humans is not clear, patients should minimize exposure to sunlight or artificial ultraviolet irradiation sources [see Warnings and Precautions (5.2)].

The genotoxic potential of tretinoin was evaluated in the Ames assay and in the in vivo mouse micronucleus assay, both of which were negative.

The components of the microspheres have shown potential for genetic toxicity and fetal malformation. EGDMA, a component of the excipient acrylates copolymer, was positive for induction of structural chromosomal aberrations in the in vitro chromosomal aberration assay in mammalian cells in the absence of metabolic activation, and negative for genetic toxicity in the Ames assay, and the in vivo mouse micronucleus assay.

In oral fertility studies in rats with tretinoin, the no-observable effect level was 2 mg/kg/day (19 times the MRHD based on BSA comparison).

14 CLINICAL STUDIES

14.1 Tretinoin gel (microsphere), 0.1%

In two vehicle-controlled trials, tretinoin gel (microsphere), 0.1%, applied once daily was significantly more effective than vehicle in reducing the acne lesion counts. The mean reductions in lesion counts from baseline after treatment for 12 weeks are shown in the following table:

Table 1: Mean Percent Reductionin Lesion Counts Tretinoin Gel (Microsphere),0.1%

 | Tretinoin gel (microsphere),0.1% |  | Vehicle Gel
 | Study#1 72 pts | Study#2 71 pts | Study#1 72 pts | Study#2 67 pts
Non-inflammatory lesion counts | 49% | 32% | 22% | 3%
Inflammatory lesion counts | 37% | 29% | 18% | 24%
Total lesion counts | 45% | 32% | 23% | 16%

Tretinoin gel (microsphere,) 0.1%, was also significantly superior to the vehicle in the investigator's global evaluation of the clinical response. In Study #1, thirty-five percent (35%) of subjects using tretinoin gel (microsphere,) 0.1%, achieved an excellent result, as compared to eleven percent (11%) of subjects on the vehicle control. In Study #2, twenty-eight percent (28%) of patients using tretinoin gel (microsphere), 0.1%, achieved an excellent result, as compared to nine percent (9%) of the subjects on the vehicle control.

14.2 Tretinoin gel (microsphere), 0.04%

In two vehicle-controlled clinical trials, tretinoin gel (microsphere), 0.04%, applied once daily, was more effective (p<0.05) than vehicle in reducing the acne lesion counts. The mean reductions in lesion counts from baseline after treatment for 12 weeks are shown in the following table:

Table 2: Mean Percent Reductionin Lesion Counts Tretinoin gel (microsphere),0.04%

 | Tretinoin gel (microsphere),0.04% |  | Vehicle Gel
 | Study#3 108 pts | Study#4 111 pts | Study#3 110 pts | Study#4 103 pts
Non-inflammatory lesion counts | 37% | 29% | −2%* | 14%
Inflammatory lesion counts | 44% | 41% | 13% | 30%
Total lesion counts | 40% | 35% | 8% | 20%

* - That is, a mean percent increase of 2%

Tretinoin gel (microsphere,) 0.04%, was also superior (p<0.05) to the vehicle in the investigator's global evaluation of the clinical response. In Study #3, fourteen percent (14%) of subjects using tretinoin gel (microsphere,) 0.04%, achieved an excellent result compared to five percent (5%) of subjects on vehicle control. In Study #4, nineteen percent (19%) of subjects using tretinoin gel (microsphere), 0.04%, achieved an excellent result compared to nine percent (9%) of subjects on vehicle control.

16 HOW SUPPLIED/STORAGE AND HANDLING

16.1 How Supplied

Tretinoin gel (microsphere) is opaque and white to very pale yellow in color.
Tretinoin gel (microsphere), 0.08%, is supplied in 50 gram pump (NDC 21922-043-40).

16.2 Storage Conditions

Store at 20° to 25°C (68° to 77°F); excursions permitted from 15° to 30°C (59° to 86°F) [see USP Controlled Room Temperature].

Store pump upright.

Keep out of reach of children.

17 PATIENT COUNSELING INFORMATION

Advise the patient to read the FDA-approved patient labeling (Patient Information).

The patient should be instructed to:

Cleanse the treatment area thoroughly, before treatment, with a mild, non-medicated cleanser. Do not use more than the recommended amount and do not apply tretinoin gel (microsphere) more than once daily as this will not produce faster or better results, but may increase irritation.

Minimize exposure to sunlight, including sunlamps. Recommend the use of sunscreen products and protective apparel (e.g., hat) when exposure cannot be avoided.

Made in Italy, formulated in India

Manufactured by:
Encube Ethicals Pvt. Ltd.

Plot No. C-1, Madkaim Industrial Estate,

Madkaim, Post: Mardol, Ponda,

Goa-403 404, India.

Distributed by:
Encube Ethicals, Inc.
200 Meredith Drive, Suite 202
Durham, NC 27713 USA

Patient Information
Tretinoin Gel (microsphere)

(truh•ti•now•uhn)
Tretinoin Gel (microsphere) 0.08%

for topical use

Important information: Tretinoin gel (microsphere) is for use on skin only. Do not get tretinoin gel (microsphere) in your eyes, mouth, vagina or the corners of your nose.

What is Tretinoin gel (microsphere)?
Tretinoin gel (microsphere) is a prescription medicine used on the skin (topical) to treat acne. Acne is a condition in which the skin has blackheads, whiteheads, and other pimples.
It is not known if tretinoin gel (microsphere) is safe and effective in the treatment of other conditions.
It is not known if tretinoin gel (microsphere) is safe and effective in children under 12 years of age.

What should I tell my doctor before using tretinoin gel (microsphere)?
Before using tretinoin gel (microsphere), tell your doctor about all of your medical conditions, including if you:

- have a skin condition called eczema.
- have a sunburn. You should not use tretinoin gel (microsphere) until your skin has healed.
- have any other medical condition.
- are pregnant or plan to become pregnant. It is not known if tretinoin gel (microsphere) will harm your unborn baby.
- are breastfeeding or plan to breastfeed. It is not known if tretinoin gel (microsphere) passes into your breast milk.

Tell your doctor about all of the medicines you take, including prescription and over-the counter medicines, vitamins, herbal supplements, and any skin products that you use.
Especially tell your doctor if you use any other medicines to treat your acne, including medicated cleansers or soaps. Using other topical acne products may increase the irritation of your skin when used with tretinoin gel (microsphere).
Know the medicines you take. Keep a list of them to show your doctor and pharmacist when you get a new medicine.

How should I use tretinoin gel (microsphere)?

- Use tretinoin gel (microsphere) exactly as your doctor tells you to use it.
- Your doctor may change your dose of tretinoin gel (microsphere) if you have skin irritation.
- Before you apply tretinoin gel (microsphere), gently wash the affected skin area with a mild, non-medicated soap. Rinse and pat your skin dry.
- Apply tretinoin gel (microsphere) 1 time a day in the evening, or as prescribed by your doctor.
- Do not use more tretinoin gel (microsphere) than you need to cover the affected area and do not apply tretinoin gel (microsphere) more than 1 time a day. Using too much tretinoin gel (microsphere) or using it too often will not give you faster or better results, and you may get skin redness, peeling, or discomfort.
- You may have a brief feeling of warmth or slight stinging after applying tretinoin gel (microsphere).
- You may use moisturizers and cosmetics.
- Early in your treatment, you may get new pimples. At this stage, it is important to continue using tretinoin gel (microsphere).
- Your acne may not get better right away. Use tretinoin gel (microsphere) even after your acne improves. Your acne may get better after two weeks of treatment, but more than seven weeks of tretinoin gel (microsphere) treatment are needed before you get the full benefit.

Applying tretinoin gel (microsphere):

- Tretinoin gel (microsphere) comes in a pump. If you have been prescribed the:

Pump: Fully depress the pump twice to dispense tretinoin gel (microsphere) onto a fingertip. Apply a thin layer to cover the affected area, as prescribed by your doctor. Spread tretinoin gel (microsphere) evenly over the affected area.

- Wash your hands after applying tretinoin gel (microsphere).

What should I avoid while using tretinoin gel (microsphere)?

- Avoid washing your skin too often and scrubbing the affected skin area.
- You should avoid sunlamps, tanning beds, and ultraviolet light during treatment with tretinoin gel (microsphere).
- Minimize exposure to sunlight.
- If you have to be in the sunlight or are sensitive to sunlight, use a sunscreen with SPF (sun protection factor) of 15 or more and wear a wide-brimmed hat or other protective clothing to cover the treated areas.
- If you do get sunburned, stop using tretinoin gel (microsphere) until your skin has healed and is back to normal.
- Cold weather and wind may irritate skin treated with tretinoin gel (microsphere). Talk to your doctor about ways to manage skin irritation.
- Avoid contact with the peels of limes.

What are the possible side effects of tretinoin gel (microsphere)?
Tretinoin gel (microsphere) may cause serious side effects, including:
Skin irritation. Tretinoin gel (microsphere) may cause skin dryness, redness, swelling, and blistering. If you develop these symptoms, your doctor may tell you to stop using tretinoin gel (microsphere) for a while, change your dose, decrease the number of times you apply tretinoin gel (microsphere),or completely stop treatment with tretinoin gel (microsphere). It is not known if tretinoin gel (microsphere) is effective when used less than 1 time a day.

The most common side effects of tretinoin gel (microsphere) include skin burning and itching.

Tell your doctor if you have any side effect that bothers you or that does not go away.
These are not all the possible side effects of tretinoin gel (microsphere). For more information, ask your doctor or pharmacist.
Call your doctor for medical advice about side effects. You may report side effects to FDA at 1-800- FDA-1088.

How should I store tretinoin gel (microsphere)?

- Store tretinoin gel (microsphere) at room temperature between 68°F to 77°F (20°C to 25°C).
- Store tretinoin gel (microsphere) pump upright.

Keep tretinoin gel (microsphere) and all medicines out of the reach of children.

General information about the safe and effective use of tretinoin gel (microsphere).
Medicines are sometimes prescribed for purposes other than those listed in a Patient Information leaflet. Do not use tretinoin gel (microsphere) for a condition for which it was not prescribed. Do not give tretinoin gel (microsphere) to other people, even if they have the same symptoms you have. It may harm them.

If you would like more information, talk with your doctor. You can ask your pharmacist or doctor for information about tretinoin gel (microsphere) that is written for health professionals.

For more information, call 1-833-285-4151.

What are the ingredients of tretinoin gel (microsphere)?
Active ingredient: tretinoin

Inactive ingredients: benzyl alcohol, butylated hydroxytoluene, carbomer 974P, cyclomethicone and dimethicone copolyol, disodium EDTA, glycerin, PPG-20 methyl glucose ether distearate, propylene glycol, propylene glycol dicaprylate/dicaprate, purified water, sorbic acid and trolamine.

This Patient Information has been approved by the U.S. Food and Drug Administration.

Made in Italy, formulated in India

Manufactured by:
Encube Ethicals Pvt. Ltd.
Plot No. C-1, Madkaim Industrial Estate,

Madkaim, Post: Mardol, Ponda,

Goa-403 404, India.

Distributed by:
Encube Ethicals, Inc.
200 Meredith Drive, Suite 202
Durham, NC 27713 USA
Revised- 08/2023

PACKAGE LABEL.PRINCIPAL DISPLAY PANEL

CARTON LABEL 0.08% for 50gm

NDC 21922-043-40

Tretinoin Gel

(Microsphere),

0.08%

PUMP

For Topical Use Only

Net wt. 50 g

Rx only